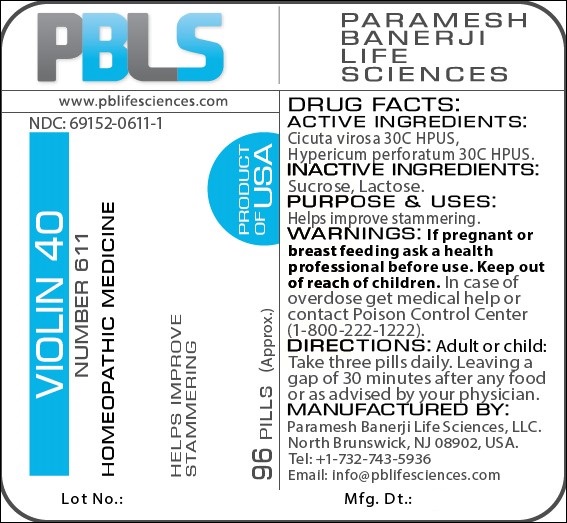 DRUG LABEL: Violin 40 Number 611
NDC: 69152-0611 | Form: PELLET
Manufacturer: Paramesh Banerji Life Sciences LLC
Category: homeopathic | Type: HUMAN OTC DRUG LABEL
Date: 20171106

ACTIVE INGREDIENTS: HYPERICUM PERFORATUM 30 [hp_C]/1 1; CICUTA VIROSA ROOT 30 [hp_C]/1 1
INACTIVE INGREDIENTS: SUCROSE; LACTOSE

DRUG FACTS: Active Ingredients

Cicuta virosa 30C HPUS, Hypericum perforatum 30C HPUS

Inactive Ingredients

Sucrose, Lactose

Purpose

Helps improve stammering

Uses

Helps improve stammering

Warnings

If pregnant or breast feeding ask a health professional before use.

Keep out of reach of children. In case of overdose, get medical help or contact a Poison Control Center (1-800-222-1222) right away.

Direction

Adult or child: Take three pills daily. Leaving a gap of 30 minutes after any food or as advised by your physician.

Manufactured by

Paramesh Banerji Life Sciences, LLC.

North Brunswick, NJ 08902, USA.

Tel: +1-732-743-5936

Email: info@pblifesciences.com

Principal Display Panel

NDC: 69152-0611-1

Violin 40

Number 611

Homeopathic Medicine

Helps improve stammering

96 Pills (Approx.)

Product of USA